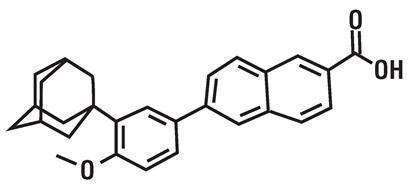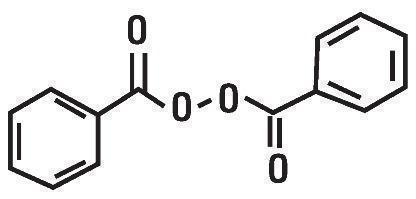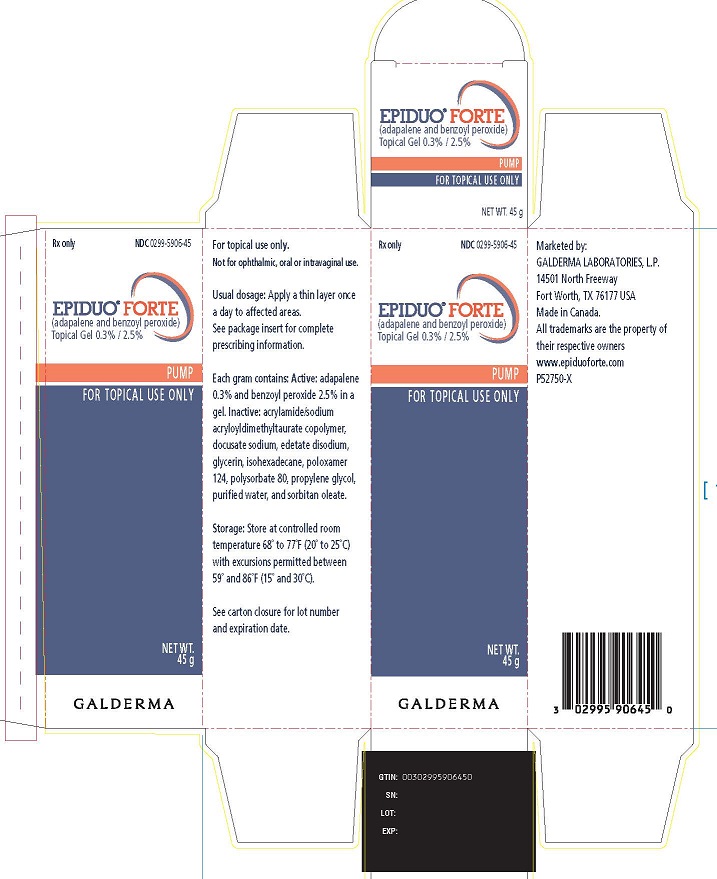 DRUG LABEL: epiduo forte
NDC: 0299-5906 | Form: GEL
Manufacturer: Galderma Laboratories, L.P.
Category: prescription | Type: HUMAN PRESCRIPTION DRUG LABEL
Date: 20241024

ACTIVE INGREDIENTS: ADAPALENE 3 mg/1 g; BENZOYL PEROXIDE 25 mg/1 g
INACTIVE INGREDIENTS: ACRYLIC ACID/SODIUM ACRYLATE COPOLYMER (1:1; 600 MPA.S AT 0.2%); DOCUSATE SODIUM; EDETATE DISODIUM; GLYCERIN; ISOHEXADECANE; POLOXAMER 124; POLYSORBATE 80; PROPYLENE GLYCOL; WATER; SORBITAN MONOOLEATE

HIGHLIGHTS OF PRESCRIBING INFORMATION

These highlights do not include all the information needed to use EPIDUO FORTE safely and effectively. See full prescribing information for EPIDUO FORTE.
EPIDUO®FORTE (adapalene and benzoyl peroxide) topical gel.
Initial U.S. Approval: 2015

1 INDICATIONS AND USAGE

EPIDUO FORTE, is a combination of adapalene, a retinoid, and benzoyl peroxide and is indicated for the topical treatment of acne vulgaris in adults and pediatric patients 12 years of age and older. (1)

2 DOSAGE AND ADMINISTRATION

- For topical use only
- EPIDUO FORTE is not for oral, ophthalmic or intravaginal use. (2)
- Apply a thin layer of EPIDUO FORTE to affected areas of the face and/or trunk once daily after washing. (2)
- Use a pea-sized amount for each area of the face (e.g., forehead, chin, each cheek). (2)
- Avoid the eyes, lips, and mucous membranes. (2)

3 DOSAGE FORMS AND STRENGTHS

Topical Gel, 0.3%/2.5% (3)

4 CONTRAINDICATIONS

EPIDUO FORTE is contraindicated in patients with a history of hypersensitivity reactions to benzoyl peroxide or any components of the formulation in EPIDUO FORTE. (4)

5 WARNINGS AND PRECAUTIONS

- Hypersensitivity:Severe hypersensitivity reactions, including anaphylaxis and angioedema, have been reported with the use of benzoyl peroxide products. (5.1)
- Photosensitivity:Avoid exposure to sunlight and sunlamps. Wear broad spectrum sunscreen and protective clothing when sun exposure cannot be avoided. (5.2)
- Skin Irritation:Erythema, scaling, dryness, stinging/burning, irritant and allergic contact dermatitis may occur with use of EPIDUO FORTE and may necessitate discontinuation. (5.3)

6 ADVERSE REACTIONS

The most common adverse reactions (incidence ≥1%) are skin irritation, eczema, atopic dermatitis and skin burning sensation. (6)

To report SUSPECTED ADVERSE REACTIONS, contact Galderma Laboratories, L.P. at 1-866-735-4137 or FDA at
1-800-FDA-1088 or www.fda.gov/medwatch .

FULL PRESCRIBING INFORMATION

1 INDICATIONS AND USAGE

EPIDUO FORTE is indicated for the topical treatment of acne vulgaris in adults and pediatric patients 12 years of age and older.

2 DOSAGE AND ADMINISTRATION

- For topical use only. EPIDUO FORTE is not for oral, ophthalmic, or intravaginal use.
- Apply a thin layer of EPIDUO FORTE to affected areas of the face and/or trunk once daily after washing.
- Use a pea-sized amount for each area of the face (e.g., forehead, chin, each cheek).
- Wash hands after application as EPIDUO FORTE may bleach hair or colored fabrics.
- Avoid the eyes, lips and mucous membranes.

3 DOSAGE FORMS AND STRENGTHS

Each gram of EPIDUO FORTE topical gel contains 3 mg (0.3%) adapalene and 25 mg (2.5%) benzoyl peroxide in a white to very pale yellow, opaque gel. EPIDUO FORTE is available in pumps containing 15 g, 30 g, 45 g, 60 g or 70 g.

4 CONTRAINDICATIONS

EPIDUO FORTE is contraindicated in patients with a history of hypersensitivity reactions to benzoyl peroxide or any components of the formulation in EPIDUO FORTE.

5 WARNINGS AND PRECAUTIONS

5.1 Hypersensitivity

Hypersensitivity reactions, including anaphylaxis, angioedema, and urticaria, have been reported with the use of benzoyl peroxide products. If a serious hypersensitivity reaction occurs, discontinue EPIDUO FORTE immediately and initiate appropriate therapy.

5.2 Photosensitivity

Avoid exposure to sunlight, including sunlamps, during the use of EPIDUO FORTE. Patients with high levels of sun exposure and those with inherent sensitivity to sun should exercise particular caution. Use of broad spectrum sunscreen products and protective apparel (e.g., hat) are recommended when exposure cannot be avoided. Weather extremes, such as wind or cold, may be irritating to patients under treatment with EPIDUO FORTE.

5.3 Skin Irritation/Contact Dermatitis

Erythema, scaling, dryness, and stinging/burning may be experienced with use of EPIDUO FORTE. These are most likely to occur during the first four weeks of treatment, are mostly mild to moderate in intensity, and usually lessen with continued use of the medication. Irritant and allergic contact dermatitis may occur. Depending upon the severity of these adverse reactions, patients should be instructed to use a moisturizer, reduce the frequency of the application of EPIDUO FORTE, or discontinue use. The product should not be applied to cuts, abrasions, eczematous or sunburned skin. As with other retinoids, use of “waxing” as a depilatory method should be avoided on skin treated with EPIDUO FORTE.
Avoid concomitant use of other potentially irritating topical products (medicated or abrasive soaps and cleansers, soaps and cosmetics that have strong skin-drying effect and products with high concentrations of alcohol, astringents, spices or limes).

6 ADVERSE REACTIONS

6.1 Clinical Trials Experience

The following adverse reactions are discussed in greater detail elsewhere in the labeling:

- Hypersensitivity [ see Warnings and Precautions (5.1) ]
- Skin Irritation/Contact Dermatitis [ see Warnings and Precautions (5.3) ]

Because clinical studies are conducted under widely varying conditions, adverse reaction rates observed in the clinical studies of a drug cannot be directly compared to rates in the clinical studies of another drug and may not reflect the rates observed in practice.
During the randomized, double-blind, vehicle- and active-controlled clinical trial, 217 subjects were exposed to EPIDUO FORTE. A total of 197 subjects with acne vulgaris, 12 years and older, were treated once daily for 12 weeks. Adverse reactions reported within 12 weeks of treatment in at least 1% of subjects treated with EPIDUO FORTE and for which the rate with EPIDUO FORTE exceeded the rate for the vehicle are presented in Table 1:

Table 1. Adverse Reactions Occurring in ≥ 1% of Subjects with Acne Vulgaris in a 12-week Clinical Trial
 | EPIDUO FORTE (N=217) | Adapalene and Benzoyl Peroxide Gel, 0.1%/2.5% (N=217) | Vehicle (N=69)
Skin irritation | 4% | <1% | 0%
Eczema | 1% | 0% | 0%
Dermatitis atopic | 1% | 0% | 0%
Skin burning sensation | 1% | 0% | 0%

Local tolerability evaluations presented in Table 2, were conducted at each trial visit in the clinical trial by assessment of erythema, scaling, dryness, and stinging/burning, which peaked at Week 1 of therapy and decreased thereafter.

Table 2. Incidence of Local Cutaneous Irritation in 12-week Clinical Trial in Subjects with Acne Vulgaris
 | Maximum Severity During Treatment |  | End of Treatment Severity (Final Score)
 | Moderate | Severe | Moderate | Severe
EPIDUO FORTE (N=213)
Erythema | 20% | 1% | 4% | <1%
Scaling | 17% | 1% | 1% | <1%
Dryness | 15% | 2% | 3% | <1%
Stinging/Burning | 19% | 6% | 1% | 1%
Adapalene and Benzoyl Peroxide Gel, 0.1%/2.5% (N=212)
Erythema | 15% | 1% | 2% | <1%
Scaling | 12% | <1% | 2% | 0%
Dryness | 13% | 1% | 2% | 0%
Stinging/Burning | 14% | 9% | 3% | 0%
Vehicle (N=68)
Erythema | 6% | 1% | 1% | 0%
Scaling | 6% | 0% | 1% | 0%
Dryness | 4% | 1% | 1% | 0%
Stinging/Burning | 3% | 1% | 0% | 0%

6.2 Postmarketing Experience

The following adverse reactions have been identified during postapproval use of EPIDUO FORTE. Because these reactions are reported voluntarily from a population of uncertain size, it is not always possible to reliably estimate their frequency or establish a causal relationship to drug exposure.
Skin and subcutaneous tissue disorders: sunburn, blister (including vesicles and bullae), pruritus, hyperpigmentation and hypopigmentation..

8 USE IN SPECIFIC POPULATIONS

8.1 Pregnancy

Risk Summary
Available pharmacovigilance data with EPIDUO FORTE use in pregnant women are insufficient to establish a drug associated risk of major birth defects, miscarriage or other adverse maternal or fetal outcomes. Animal reproduction studies have not been conducted with the combination gel.

Adapalene gel, 0.3%
Available data from clinical trials with adapalene gel 0.3% use in pregnant women are insufficient to establish a drug-associated risk of major birth defects, miscarriage or other adverse maternal or fetal outcomes. In animal reproduction studies, oral administration of adapalene to pregnant rats and rabbits during organogenesis at dose exposures 41 and 81 times, respectively, the human exposure at the maximum recommended human dose (MRHD) of 2 g resulted in fetal skeletal and visceral malformations (see Data).

Benzoyl peroxide gel, 2.5%
The systemic exposure of benzoyl peroxide is unknown. Based on published literature, benzoyl peroxide is rapidly metabolized to benzoic acid (an endogenous substance), which is eliminated in the urine. Hence, maternal use is not expected to result in fetal exposure of the drug.
The background risk of major birth defects and miscarriage for the indicated population is unknown. All pregnancies have a background risk of birth defect, loss, or other adverse outcomes. In the U.S. general population, the estimated risk of major birth defects and miscarriage in clinically recognized pregnancies is 2 to 4% and 15 to 20%, respectively.

Data
Animal Data
No malformations were observed in rats treated with oral adapalene doses of 0.15 to 5.0 mg/kg/day, up to 8 times the MRHD of 2 grams of EPIDUO FORTE based on a mg/m2 comparison. However, malformations were observed in rats and rabbits when treated with oral doses of ≥ 25 mg/kg/day adapalene (41 and 81 times the MRHD, respectively, based on a mg/m2 comparison). Findings included cleft palate, microphthalmia, encephalocele, and skeletal abnormalities in rats and umbilical hernia, exophthalmos, and kidney and skeletal abnormalities in rabbits.
Dermal adapalene embryofetal development studies in rats and rabbits at doses up to 6.0 mg/kg/day (9.7 and 19.5 times the MRHD, respectively, based on a mg/m2 comparison) exhibited no fetotoxicity and only minimal increases in skeletal variations (supernumerary ribs in both species and delayed ossification in rabbits).

8.2 Lactation

Risk Summary
Adapalene gel, 0.3%
There are no data on the presence of adapalene topical gel or its metabolite in human milk, the effects on the breastfed infant, or the effects on milk production. In animal studies, adapalene is present in rat milk with oral administration of the drug. When a drug is present in animal milk, it is likely that the drug will be present in human milk. It is possible that topical administration of large amounts of adapalene could result in sufficient systemic absorption to produce detectable quantities in human milk (see Clinical Considerations).
Benzoyl peroxide gel, 2.5%
The systemic exposure of benzoyl peroxide is unknown. Based on the published literature, benzoyl peroxide is rapidly metabolized to benzoic acid (an endogenous substance), which is eliminated in the urine. Any amount of benzoyl peroxide excreted into human milk by a nursing mother would be expected to be rapidly metabolized by tissue and stomach esterases. There are no data on the presence of benzoyl peroxide in human milk, its effects on the breastfed infant or its effects on milk production.
The developmental and health benefits of breastfeeding should be considered along with the mother's clinical need for EPIDUO FORTE and any potential adverse effects on the breastfed child from EPIDUO FORTE or from the underlying maternal condition.
Clinical Considerations
To minimize potential exposure to the breastfed infant via breastmilk, use EPIDUO FORTE on the smallest area of skin and for the shortest duration possible while breastfeeding. Advise breastfeeding women not to apply EPIDUO FORTE directly to the nipple and areola to avoid direct infant exposure.

8.4 Pediatric Use

Safety and effectiveness of EPIDUO FORTE in pediatric patients under the age of 12 have not been established.

8.5 Geriatric Use

Clinical studies of EPIDUO FORTE did not include sufficient numbers of subjects aged 65 years and over to determine whether they respond differently from younger subjects.

11 DESCRIPTION

EPIDUO FORTE (adapalene and benzoyl peroxide) topical gel, 0.3%/2.5% is a white to very pale yellow, opaque gel for topical use containing adapalene 0.3% and benzoyl peroxide 2.5%.
Adapalene, a synthetic retinoid, is a naphthoic acid derivative with retinoid-like properties. The chemical name for adapalene is (6-[3-(1-adamantyl)-4-methoxyphenyl]-2-naphthoic acid). It has the following structural formula:

Adapalene:

Molecular formula: C28H28O3Molecular weight: 412.5

Benzoyl Peroxide is a highly lipophilic oxidizing agent that localizes in both bacterial and keratinocyte cell membranes. The chemical name for benzoyl peroxide is dibenzoyl peroxide. It has the following structural formula:

Benzoyl Peroxide:

Molecular formula: C14H10O4Molecular weight: 242.23

EPIDUO FORTE gel contains the following inactive ingredients: acrylamide/sodium acryloyldimethyltaurate copolymer, docusate sodium, edetate disodium, glycerin, isohexadecane, poloxamer 124, polysorbate 80, propylene glycol, purified water, and sorbitan oleate.

12 CLINICAL PHARMACOLOGY

12.1 Mechanism of Action

Adapalene

Adapalene binds to specific retinoic acid nuclear receptors but does not bind to cytosolic receptor protein. Biochemical and pharmacological profile studies have demonstrated that adapalene is a modulator of cellular differentiation, keratinization and inflammatory processes. However, the significance of these findings with regard to the mechanism of action of adapalene for the treatment of acne is unknown.

Benzoyl peroxide

Benzoyl peroxide is an oxidizing agent with bactericidal and keratolytic effects.

12.2 Pharmacodynamics

Pharmacodynamics of EPIDUO FORTE is unknown.

12.3 Pharmacokinetics

A pharmacokinetic trial was conducted in 26 adult and adolescent subjects (12 to 33 years of age) with severe acne vulgaris who were treated with once-daily applications during a 4-week period with, on average, 2.3 grams/day (range 1.6 - 3.1 grams/day) of EPIDUO FORTE applied as a thin layer to the face, shoulders, upper chest and upper back. After a 4-week treatment, 16 subjects (62%) had quantifiable adapalene plasma concentrations above the limit of quantification of 0.1 ng/mL, with a mean Cmaxof 0.16 ± 0.08 ng/mL and a mean AUC0-24hrof 2.49 ± 1.21 ng.h/mL. The most exposed subject had adapalene Cmaxand AUC0-24hrof 0.35 ng/mL and 6.41 ng.h/mL, respectively. Excretion of adapalene appears to be primarily by the biliary route. Benzoyl peroxide is absorbed by the skin where it is converted to benzoic acid and eliminated in the urine.

Drug Interactions
No formal drug-drug interaction studies were conducted with EPIDUO FORTE.

13. NONCLINICAL TOXICOLOGY

13.1 Carcinogenesis, Mutagenesis, Impairment of Fertility

No carcinogenicity, genotoxicity, or fertility studies were conducted with EPIDUO FORTE.

Carcinogenicity studies with adapalene were conducted in mice at topical doses of 0.4, 1.3, and 4.0 mg/kg/day (1.2, 3.9, and 12 mg/m^2/day) and in rats at oral doses of 0.15, 0.5, and 1.5 mg/kg/day (0.9, 3.0, and 9.0 mg/m^2/day). The highest dose levels are 3.2 (mice) and 2.4 (rats) times the MRHD of EPIDUO FORTE based on a mg/m^2comparison. In the rat study, an increased incidence of benign and malignant pheochromocytomas reported in the adrenal medulla of male rats was observed.

No significant increase in tumor formation was observed in rodents topically treated with 15-25% benzoyl peroxide carbopol gel (6-10 times the concentration of benzoyl peroxide in EPIDUO FORTE) for two years. Rats received maximum daily applications of 138 (males) and 205 (females) mg/kg benzoyl peroxide (27-40 times the MRHD based on a mg/m^2comparison). Similar results were obtained in mice topically treated with 25% benzoyl peroxide carbopol gel for 56 weeks followed by intermittent treatment with 15% benzoyl peroxide carbopol gel for rest of the 2 year study period, and in mice topically treated with 5% benzoyl peroxide carbopol gel for two years.

Benzoyl peroxide is a tumor promoter in several animal species. The significance of this finding in humans is unknown.

Adapalene was not mutagenic or genotoxic in vitro(Ames test, Chinese hamster ovary cell assay, or mouse lymphoma TK assay) or in vivo(mouse micronucleus test).

Benzoyl peroxide caused DNA strand breaks and DNA-protein cross-links in mammalian cells, increased sister chromatid exchanges in Chinese hamster ovary cells, and was mutagenic in a few, but not all, in vitrobacterial mutagenicity assays (Ames tests) conducted.

In rat oral studies, 20 mg/kg/day adapalene (32 times the MRHD based on a mg/m^2comparison) did not affect the reproductive performance and fertility of F0males and females or the growth, development, or reproductive function of F1offspring.

No fertility studies were conducted with benzoyl peroxide.

14 CLINICAL STUDIES

The safety and efficacy of EPIDUO FORTE applied once daily for 12 weeks for the treatment of acne vulgaris were assessed in a multicenter, randomized, double-blind, vehicle-controlled trial, comparing EPIDUO FORTE to vehicle gel in subjects with acne vulgaris. The trial also evaluated adapalene and benzoyl peroxide gel, 0.1%/2.5%, a lower strength product than EPIDUO FORTE (adapalene and benzoyl peroxide) topical gel, 0.3%/2.5%. In this trial, 217 subjects were treated with EPIDUO FORTE, 217 subjects with adapalene and benzoyl peroxide, gel, 0.1%/2.5% and 69 subjects with the vehicle gel.

Treatment response was defined as the percent of subjects who were rated “clear” or “almost clear’ at Week 12 with at least a two-grade improvement based on the Investigator’s Global Assessment (IGA), and mean absolute change from baseline at Week 12 in both inflammatory and non-inflammatory lesion counts. An IGA score of ‘Clear’ corresponded to clear skin with no inflammatory or non-inflammatory lesions. An IGA score of “almost clear” corresponded to a few scattered comedones and a few small papules.

At baseline, 50% of subjects were graded as “moderate” (IGA Grade 3) and 50% were graded as “severe” (IGA Grade 4) on the IGA scale. Subjects had an average of 98 (range 51-226) total lesions of which the mean number of inflammatory lesions was 38 (range: 20-99) and the mean number of non-inflammatory lesions was 60 (range 30- 149). Subjects ranged in age from 12 to 57 years, with 273 (54%) of subjects 12 to 17 years of age. Approximately equal number of males (48%) and females (52%) were enrolled.

The IGA success rate, mean reduction, and percent reduction in acne lesion counts from baseline after 12 weeks of treatment are presented in the following table.

Table 3. Clinical Efficacy of EPIDUO FORTE at Week 12 in Subjects with Acne Vulgaris
 | EPIDUO FORTE (N=217) | Adapalene and Benzoyl Peroxide Gel, 0.1%/2.5% (N=217) * | Vehicle (N=69)
IGA: two-grade improvement and "clear" or "almost clear" | 33.7% | 27.3% | 11.0%
Inflammatory lesions: mean absolute (percent) reduction | 27.8 (68.7%) | 26.5 (69.3%) | 13.2 (39.2%)
Non-inflammatory lesions: mean absolute (percent) reduction | 40.5 (68.3%) | 40.0 (68.0%) | 19.7 (37.4%)

* This trial was not designed or powered to compare the efficacy of EPIDUO FORTE to the lower strength adapalene and benzoyl peroxide gel, 0.1%/2.5%, nor to compare the lower strength adapalene and benzoyl peroxide gel, 0.1%/2.5% to the vehicle control.

In subjects graded as “severe” (IGA Grade 4), efficacy was observed in the EPIDUO FORTE group.

16 HOW SUPPLIED/STORAGE AND HANDLING

16.1 How Supplied

EPIDUO FORTE (adapalene and benzoyl peroxide) gel 0.3%/2.5% is white to very pale yellow in color and opaque in appearance, and is supplied as follows:

15 gram pump NDC 0299-5906-15
30 gram pump NDC 0299-5906-30
45 gram pump NDC 0299-5906-45
60 gram pump NDC 0299-5906-60
70 gram pump NDC 0299-5906-70

16.2 Storage and handling

- Store at controlled room temperature 20 – 25˚C (68 – 77˚F) with excursions permitted to 15˚ – 30˚C (59˚ – 86˚F) [see USP controlled room temperature].
- Keep away from heat.
- Protect from light.
- Keep out of reach of children.

17 PATIENT COUNSELING INFORMATION

Advise the patient to read the FDA approved patient labeling (Patient Information).

Hypersensitivity
Inform patients that serious hypersensitivity reactions occurred with the use of benzoyl peroxide products. If a patient experiences a serious hypersensitivity reaction, instruct patient to discontinue EPIDUO FORTE immediately and seek medical help [ see Warnings and Precautions (5.1)].

Photosensitivity
Advise patients to minimize or avoid exposure to natural or artificial light, including tanning beds or UVA/B treatment. Recommend the use of broad spectrum sunscreen products and protective apparel (e.g., hat) when exposure cannot be avoided [ see Warnings and Precautions (5.2)].

Skin Irritation/Contact Dermatitis
Inform patients that EPIDUO FORTE may cause irritation such as erythema, scaling, dryness, stinging or burning [ see Warnings and Precautions (5.3)].

Lactation
Use EPIDUO FORTE on the smallest part of the skin and for the shortest duration possible while breastfeeding. Advise breastfeeding women not to apply EPIDUO FORTE directly to the nipple and areola to avoid direct infant exposure [ see Use in Specific Populations (8.2)].

Administration Instructions

- Advise patients to cleanse the area to be treated with a mild or soapless cleanser; pat dry. Apply EPIDUO FORTE as a thin layer, avoiding the eyes, lips and mucous membranes.
- Advise patients not to use more than the recommended amount and not to apply more than once daily as this will not produce faster results, but may increase irritation.
- Wash hands after application as EPIDUO FORTE may bleach hair and colored fabric.

Marketed by:
GALDERMA LABORATORIES, L.P.
Fort Worth, Texas 76177 USA

Made in Canada
All trademarks are the property of their respective owners.

Patient Information

EPIDUO FORTE (Ep-E-Do-Oh For-Tay)
(adapalene and benzoyl peroxide)
topical gel

Important Information:EPIDUO FORTE is for use on the skin only (topical). Do not use EPIDUO FORTE
in or on your mouth, eyes, or vagina.

What is EPIDUO FORTE?
EPIDUO FORTE is a prescription medicine used on the skin (topical) to treat acne vulgaris. It is not known whether EPIDUO FORTE is safe and effective in children under 12 years of age.

Do not use EPIDUO FORTE if youhave had an allergic reaction to benzoyl peroxide or any of the ingredients in EPIDUO FORTE. See the end of this Patient Information leaflet for a complete list of ingredients in EPIDUO FORTE.

Before using EPIDUO FORTE, tell your doctor about all of your medical conditions, including if you:

- have other skin problems, including cuts, abrasions, sunburn or eczema.
- are pregnant or plan to become pregnant. It is not known if EPIDUO FORTE can harm your unborn baby.
- are breastfeeding or plan to breastfeed. It is not known if EPIDUO FORTE passes into your breast milk and if it can harm your baby. Talk to your doctor about the best way to feed your baby if you use EPIDUO FORTE. If you use EPIDUO FORTE while breastfeeding, use EPIDUO FORTE on the smallest area of the skin and for the shortest time needed. Do not apply EPIDUO FORTE directly to the nipple and the areola to minimize contact with your baby.

Tell your doctor about all the medicines you take, including prescription and over-the-counter medicines, vitamins, and herbal supplements.

How should I use EPIDUO FORTE?

- Use EPIDUO FORTE exactly as your doctor tells you to use it.
- Apply EPIDUO FORTE 1 time a day.
- Do not use more EPIDUO FORTE than you need to cover the treatment area. Using too much EPIDUO FORTE or using it more than 1 time a day may increase your chance of skin irritation.

Applying EPIDUO FORTE:

- Wash the area where the gel will be applied with a mild or soapless cleanser and pat dry.
- EPIDUO FORTE comes in a pump. Depress the pump to dispense a small amount (about the size of a pea) of EPIDUO FORTE and spread a thin layer over the treatment area. Use a pea-sized amount for each area of the face (forehead, chin, and each cheek).
- Wash your hands right away after applying the gel. EPIDUO FORTE may bleach your hair or colored fabrics. Allow EPIDUO FORTE to dry completely before dressing to prevent bleaching of your clothes.

What should I avoid while using EPIDUO FORTE?

- Avoid spending time in sunlight or artificial sunlight, such as tanning beds or sunlamps. EPIDUO FORTE can make your skin sensitive to sun and the light from tanning beds and sunlamps. Use sunscreen and wear a hat and clothes that cover the areas treated with EPIDUO FORTE if you have to be in sunlight.
- Cold weather and wind may irritate skin treated with EPIDUO FORTE.
- Avoid applying EPIDUO FORTE to cuts, abrasions, and sunburned skin.
- Avoid skin products that may dry or irritate your skin such as medicated or harsh soaps, astringents, cosmetics that make your skin dry, and products containing high levels of alcohol, spices, or limes.
- Avoid the use of “waxing” as a hair removal method on skin treated with EPIDUO FORTE.

What are the possible side effects of EPIDUO FORTE?
EPIDUO FORTE may cause serious side effects including:

- Allergic reactions.Stop using EPIDUO FORTE and get medical help right away if you have any of the following symptoms during treatment with EPIDUO FORTE:
  - hives, rash or severe itching
  - swelling of your face, eyes, lips, tongue, or throat
  - trouble breathing or throat tightness
  - feeling faint, dizzy, or lightheaded

- Skin irritation.Skin irritation is common with EPIDUO FORTE and is most likely to happen during the first 4 weeks of treatment, and usually lessen with continued use of EPIDUO FORTE. Skin reactions at the treatment area include redness, scaling, dryness, stinging, burning, itching and swelling. Tell your doctor if you get any skin reactions.
- Sensitivity to sunlight. See “What should I avoid while using EPIDUO FORTE?”

These are not all of the possible side effects of EPIDUO FORTE.
Call your doctor for medical advice about side effects. You may report side effects to FDA at 1-800-FDA-1088.

How should I store EPIDUO FORTE?

- Store EPIDUO FORTE at room temperature between 68°F to 77°F (20°C to 25°C).
- Keep EPIDUO FORTE out of light and away from heat.

Keep EPIDUO FORTE and all medicines out of the reach of children.

General information about the safe and effective use of EPIDUO FORTE

Medicines are sometimes prescribed for purposes other than those listed in a Patient Information leaflet. Do not use EPIDUO FORTE for a condition for which it was not prescribed. Do not give EPIDUO FORTE to other people, even if they have the same symptoms you have. It may harm them. You can ask your doctor or pharmacist for information about EPIDUO FORTE that is written for health professionals.

What are the ingredients in EPIDUO FORTE?

Active ingredient:adapalene and benzoyl peroxide

Inactive ingredients:acrylamide/sodium acryloydimethyltaurate copolymer, docusate sodium, edetate disodium, glycerin, isohexadecane, polaxamer 124, polysorbate 80, propylene glycol, purified water and sorbitan oleate

Marketed by: GALDERMA LABORATORIES, L.P., Fort Worth, Texas 76177 USA
Made in Canada
All trademarks are the property of their respective owners.
For more information, call GALDERMA LABORATORIES, L.P. at 1-866-735-4137.

This Patient Information has been approved by the U.S. Food and Drug Administration.
Revised: 04/2022

LABEL - 45g Carton

Rx only NDC 0299-5906-45

EPIDUO®FORTE

(adapalene and benzoyl peroxide) Topical Gel 0.3%/2.5%

PUMP

FOR TOPICAL USE ONLY

NET WT.

45 g

GALDERMA

For topical use only. Not for ophthalmic, oral or intravaginal use.

Usual dosage:Apply a thin layer once a day to affected areas. See package insert for complete prescribing information.

Each gram contains: Active:adapalene 0.3% and benzoyl peroxide 2.5% in a gel. Inactive:acrylamide/sodium acryloyldimethyltaurate copolymer, docusate sodium, edetate disodium, glycerin, isohexadecane, poloxamer 124, polysorbate 80, propylene glycol, purified water, and sorbitan oleate.

Storage:Store at controlled room temperature 68° to 77°F (20° to 25°C) with excursions permitted between 59° and 86°F (15° and 30°C).

See carton closure for lot number and expiration date.

Marketed by:

GALDERMA LABORATORIES, L.P.

14501 North Freeway

Fort Worth, Texas 76177 USA

Made in Canada.

All trademarks are the property of their respective owners

www.epiduoforte.com

P52750-X